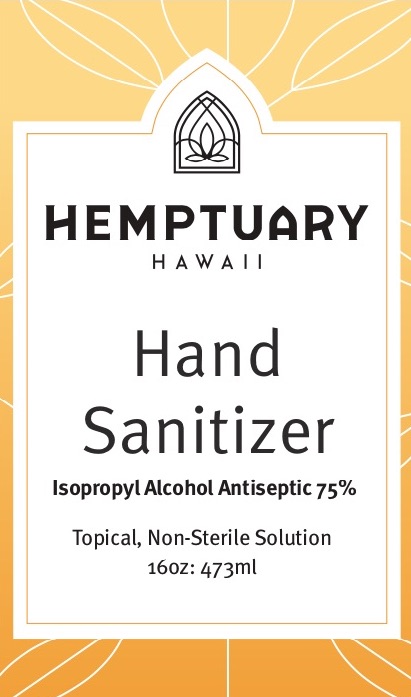 DRUG LABEL: Hemptuary Hawaii Hand Sanitizer 16 oz
NDC: 73999-001 | Form: GEL
Manufacturer: Aloha Green Holdings Inc.
Category: otc | Type: HUMAN OTC DRUG LABEL
Date: 20220113

ACTIVE INGREDIENTS: ISOPROPYL ALCOHOL 75 mL/100 mL
INACTIVE INGREDIENTS: HYDROGEN PEROXIDE 0.125 mL/100 mL; GLYCEROL FORMAL 1.45 mL/100 mL

Directions

Apply product onto hands, spread thoroughly, cover all surfaces, and rub until dry.

Supervise children children under 6 years of age when using this product to avoid swallowing.

Warnings

Flamable. Keep away from heat or flame. For external use only.

Do not ingest. If swallowed, get medical help or contact a Poison Center right away. Keep out of reach of children.

Do not use for children less than 2 months of age or on open wounds.

When using this product keep out of eyes, ears, and mouth. In case of contact with eyes, rinse eyes thoroughly with water. Stop use and ask a doctor if irritation or rash occurs. These may be signs of a serious condition.

Inactive Ingredients

glycerin, hydrogen peroxide, purified water USP

Active ingredients

Isopropyle alcohol 75% v/v

Purpose

Antiseptic

Uses

Hand santizer to help reduce bacteria that potentially can cause disease. For use when soap and water are not available.

Keep out of reach of children

Do not use for children less than 2 month sof age or on open wounds.

Front of Package

Hemptuary Hawaii Hand Santizer

Isopopoyl Alcohol Antiseptic 75% topical, non-sterile solution

16oz (473ml)